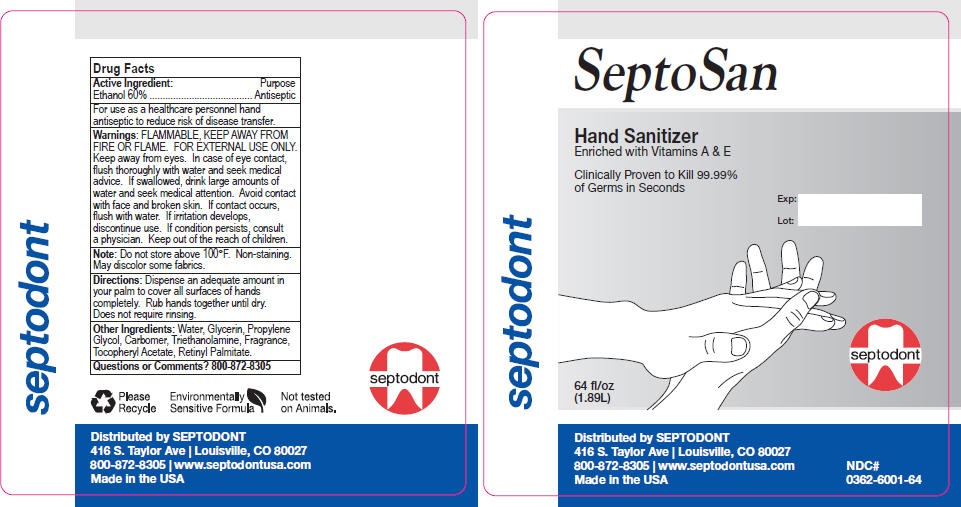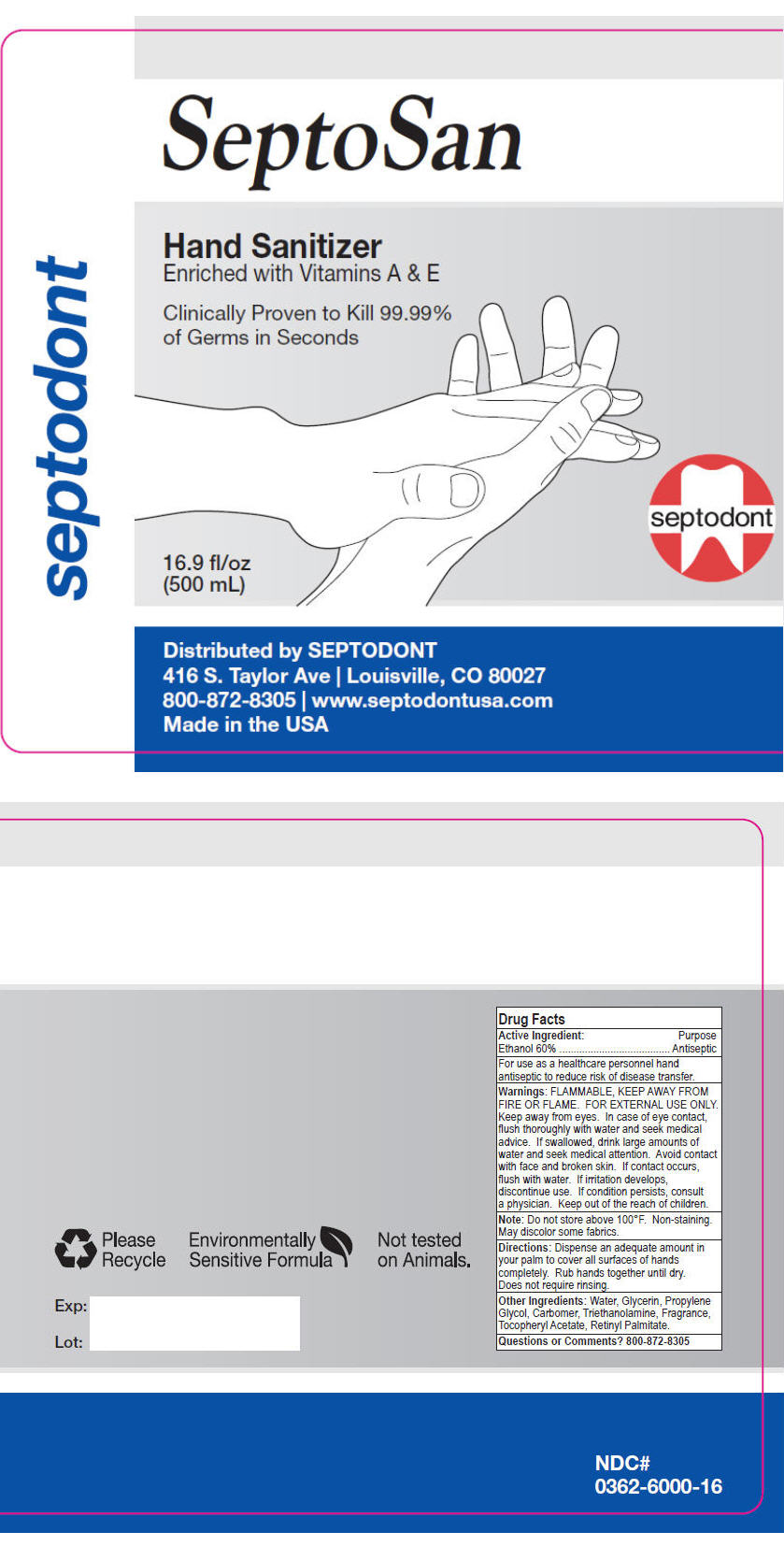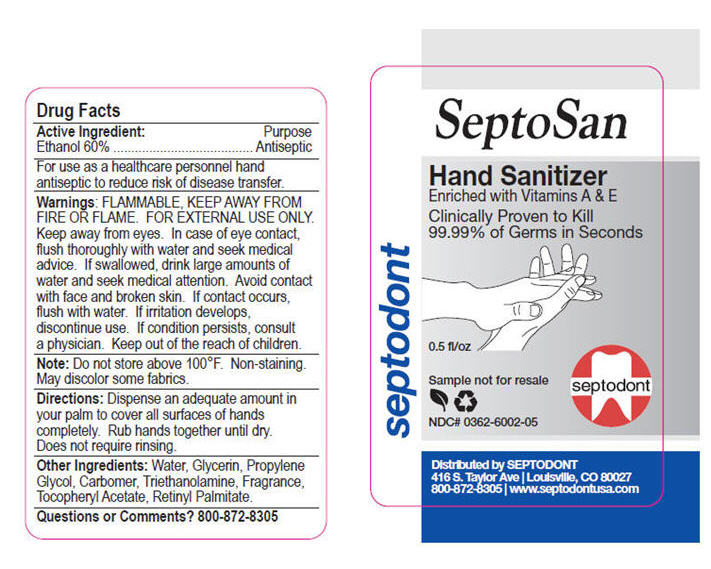 DRUG LABEL: SeptoSan 
NDC: 0362-6001 | Form: LIQUID
Manufacturer: Septodont, Inc.
Category: otc | Type: HUMAN OTC DRUG LABEL
Date: 20101006

ACTIVE INGREDIENTS: Alcohol 60 L/100 L
INACTIVE INGREDIENTS: Water; Glycerin; Propylene Glycol; Carbomer 1342; Trolamine; .ALPHA.-TOCOPHEROL ACETATE, D-; VITAMIN A PALMITATE

SeptoSan
Hand Sanitizer

Drug Facts

Active Ingredient

Ethanol 60%

Purpose

Antiseptic

INDICATIONS AND USAGE

For use as a healthcare personnel hand antiseptic to reduce risk of disease transfer.

Warnings

FLAMMABLE, KEEP AWAY FROM FIRE OR FLAME. FOR EXTERNAL USE ONLY.

WHEN USING

Keep away from eyes. In case of eye contact, flush thoroughly with water and seek medical advice. If swallowed, drink large amounts of water and seek medical attention. Avoid contact with face and broken skin. If contact occurs, flush with water.

If irritation develops, discontinue use.

ASK DOCTOR

If condition persists, consult a physician.

Keep out of the reach of children.

STORAGE AND HANDLING

Note: Do not store above 100°F. Non-staining. May discolor some fabrics.

Directions

Dispense an adequate amount in your palm to cover all surfaces of hands completely. Rub hands together until dry. Does not require rinsing.

Other Ingredients

Water, Glycerin, Propylene Glycol, Carbomer, Triethanolamine, Fragrance, Tocopheryl Acetate, Retinyl Palmitate.

Questions or Comments?

800-872-8305

Distributed by SEPTODONT
416 S. Taylor Ave | Louisville, CO 80027
800-872-8305 | www.septodontusa.com
Made in the USA

PRINCIPAL DISPLAY PANEL - 1.89L Bottle Label

septodont

SeptoSan

Hand Sanitizer
Enriched with Vitamins A & E

Clinically Proven to Kill 99.99%
of Germs in Seconds

Exp:
Lot:

64 fl/oz
(1.89L)

septodont

Distributed by SEPTODONT
416 S. Taylor Ave | Louisville, CO 80027
800-872-8305 | www.septodontusa.com
Made in the USA

NDC#
0362-6001-64

PRINCIPAL DISPLAY PANEL - 0.5 L Bottle Label

septodont

SeptoSan

Hand Sanitizer
Enriched with Vitamins A & E

Clinically Proven to Kill 99.99%
of Germs in Seconds

16.9 fl/oz
(500 mL)

septodont

Distributed by SEPTODONT
416 S. Taylor Ave | Louisville, CO 80027
800-872-8305 | www.septodontusa.com
Made in the USA

PRINCIPAL DISPLAY PANEL - 0.0148 L Bottle Label

septodont

SeptoSan

Hand Sanitizer
Enriched with Vitamins A & E

Clinically Proven to Kill
99.99% of Germs in Seconds

0.5 fl/oz

Sample not for resale

septodont

NDC# 0362-6002-05

Distributed by SEPTODONT
416 S. Taylor Ave | Louisville, CO 80027
800-872-8305 | www.septodontusa.com